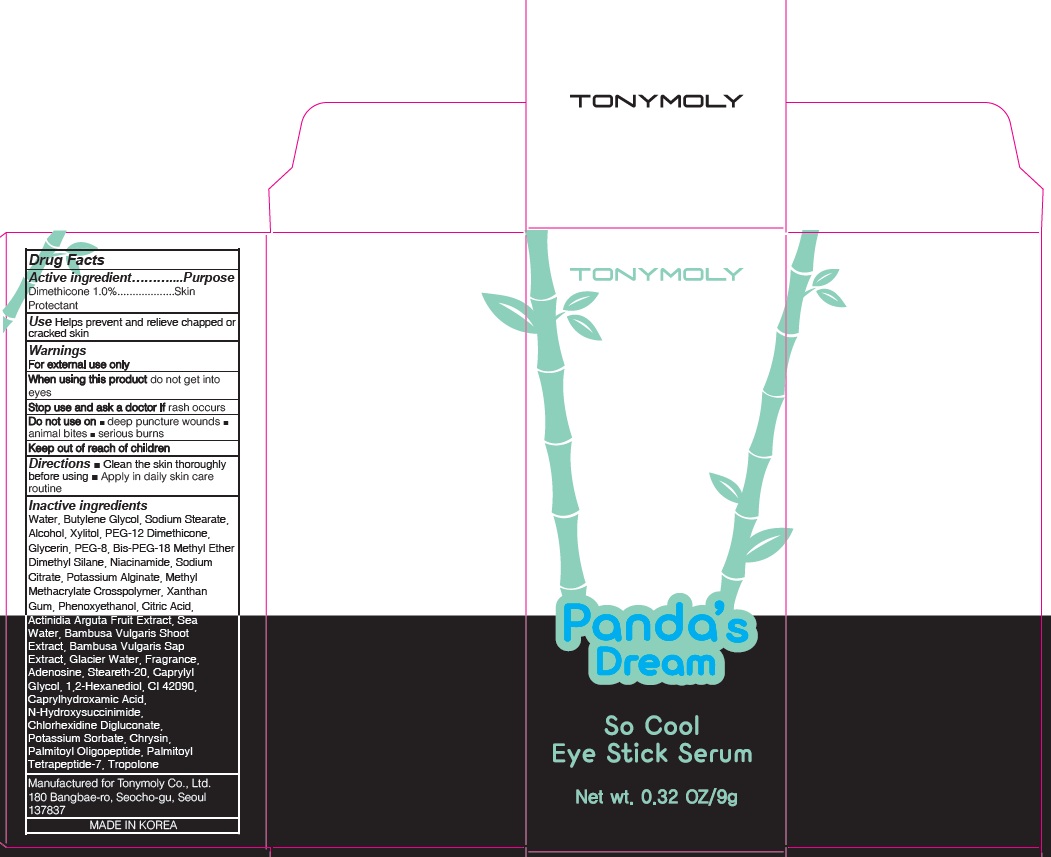 DRUG LABEL: PANDAS DREAM SO COOL EYE SERUM
NDC: 59078-314 | Form: STICK
Manufacturer: TONYMOLY CO.,LTD
Category: otc | Type: HUMAN OTC DRUG LABEL
Date: 20160616

ACTIVE INGREDIENTS: Dimethicone 0.09 g/9 g
INACTIVE INGREDIENTS: Water; Butylene Glycol

ACTIVE INGREDIENT

Active ingredient: Dimethicone 1.0%

INACTIVE INGREDIENT

Inactive Ingredient: Water, Butylene Glycol, Sodium Stearate, Alcohol, Xylitol, PEG-12 Dimethicone, Glycerin, PEG-8, Bis-PEG-18 Methyl Ether Dimethyl Silane, Niacinamide, Sodium Citrate, Potassium Alginate, Methyl Methacrylate Crosspolymer, Xanthan Gum, Phenoxyethanol, Citric Acid, Actinidia Arguta Fruit Extract, Sea Water, Bambusa Vulgaris Shoot Extract, Bambusa Vulgaris Sap Extract, Glacier Water, Fragrance, Adenosine, Steareth-20, Caprylyl Glycol, 1,2-Hexanediol, CI 42090, Caprylhydroxamic Acid, N-Hydroxysuccinimide, Chlorhexidine Digluconate, Potassium Sorbate, Chrysin, Palmitoyl Oligopeptide, Palmitoyl Tetrapeptide-7, Tropolone

PURPOSE

Purpose: Skin Protectant

WARNINGS

Warnings: For external use only When using this product do not get into eyes Stop use and ask a doctor if rash occurs Do not use on - deep puncture wounds - animal bites - serious burns Keep out of reach of children

KEEP OUT OF REACH OF CHILDREN

Use

Use: Helps prevent and relieve chapped or cracked skin

Directions

Directions: - Clean the skin thoroughly before using - Apply in daily skin care routine